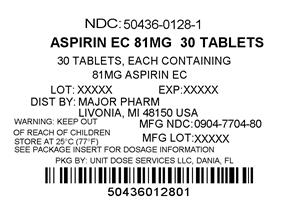 DRUG LABEL: Aspir Low
NDC: 50436-0128 | Form: TABLET
Manufacturer: Unit Dose Services
Category: otc | Type: HUMAN OTC DRUG LABEL
Date: 20120802

ACTIVE INGREDIENTS: ASPIRIN 81 mg/1 1
INACTIVE INGREDIENTS: ANHYDROUS LACTOSE; CARNAUBA WAX; SILICON DIOXIDE; CROSCARMELLOSE SODIUM; D&C YELLOW NO. 10; FERRIC OXIDE YELLOW; METHACRYLIC ACID - ETHYL ACRYLATE COPOLYMER (1:1) TYPE A; CELLULOSE, MICROCRYSTALLINE; POLYSORBATE 80; DIMETHICONE; SODIUM HYDROXIDE; SODIUM LAURYL SULFATE; TALC; TITANIUM DIOXIDE; TRIETHYL CITRATE

Drug Facts

Active ingredient

Aspirin 81 mg (NSAID*)

*nonsteroidal anti-inflammatory drug

Purpose

Pain reliever

Keep Out of Reach of Children

In case of overdose, get medical help or contact a Poison Control Center right away. Keep out of reach of children.

Uses

■ temporarily relieves minor aches and pains

■ for other uses, see your doctor, but do not use for more than 10 days without consulting your doctor because serious side effects may occur

Warnings

Children and teenagers who have or are recovering from chicken pox or flulike Reyeʼs syndrome:

symptoms should not use this product. When using this product, if changes in behavior with

nausea and vomiting occur, consult a doctor because these symptoms could be an early sign of

Reye’s syndrome; a rare but serious illness.

Aspirin may cause a severe allergic reaction, which may include: Allergy alert:

■ hives ■ facial swelling ■ shock ■ asthma (wheezing)

This product contains an NSAID, which may cause severe stomach Stomach bleeding warning:

bleeding. The chance is higher if you: ■ are age 60 or older ■ have had stomach ulcers or bleeding

problems ■ take a blood thinning (anticoagulant) or steroid drug ■ take other drugs containing

prescription or nonprescription NSAIDs (aspirin, ibuprofen, naproxen, or others) ■ have 3 or more

alcoholic drinks every day while using this product ■ take more or for a longer time than directed

■ if you are allergic to aspirin or any other pain reliever/fever reducer Do not use

■ stomach bleeding warning applies to you Ask a doctor before use if

■ you have a history of stomach problems, such as heartburn ■ you have high blood pressure,

heart disease, liver cirrhosis, or kidney disease ■ you are taking a diuretic ■ you have asthma

■ you have not been drinking fluids ■ you have lost a lot of fluid due to vomiting or diarrhea

Ask a doctor or pharmacist before use if you are

■ taking a prescription drug for diabetes, gout, or arthritis

■ under a doctor’s care for any serious condition ■ taking any other drug

■ you experience any of the following signs of stomach bleeding: Stop use and ask a doctor if

■ feel faint ■ have bloody or black stools ■ vomit blood ■ have stomach pain that does not get better

■ pain gets worse or lasts more than 10 days ■ fever gets worse or lasts more than 3 days

■ redness or swelling is present in the painful area ■ any new symptoms appear

■ ringing in the ears or a loss of hearing occurs

, ask a health professional before use. It is especially important not If pregnant or breast-feeding

to use aspirin during the last 3 months of pregnancy unless definitely directed to do so by a doctor

because it may cause problems in the unborn child or complications during delivery.

Directions

■ drink a full glass of water with each dose

■ adults and children 12 years and over: take 4 to 8 tablets every 4 hours not to exceed 48 tablets in 24 hours unless directed by a doctor

■ children under 12 years: consult a doctor

Inactive ingredients

anhydrous lactose, carnauba wax, colloidal silicon dioxide,

croscarmellose sodium, D&C yellow #10 aluminum lake, iron oxide ochre, methacrylic acid

copolymer, microcrystalline cellulose, polysorbate 80, simethicone, sodium hydroxide, sodium

lauryl sulfate, talc, titanium dioxide, triethyl citrate

Questions?

Adverse Drug Event Call: (800) 616-2471

Other Information

■ store at 25°C (77°F) excursions permitted between 15°-30°C (59°-86°F)

■ use by expiration date on package

**Compare to the active ingredient in Low Dose BAYER®

**This product is not manufactured or distributed by Bayer HealthCare LLC, owner of the registered

trademark Bayer® Low Dose.

Distributed by

Major Pharmaceuticals

31778 Enterprise Drive,

Livonia, MI 48150 USA

ASPIR LOW™

LOW STRENGTH 81mg ASPIRIN (NSAID)

Enteric Coated

1 1/4 gr. (81 mg) each Analgesic

SEE NEWWARNINGSINFORMATION

NEWTablet Appearance

THIS PACKAGE FOR HOUSEHOLDS WITHOUT YOUNG CHILDREN

MAJOR®